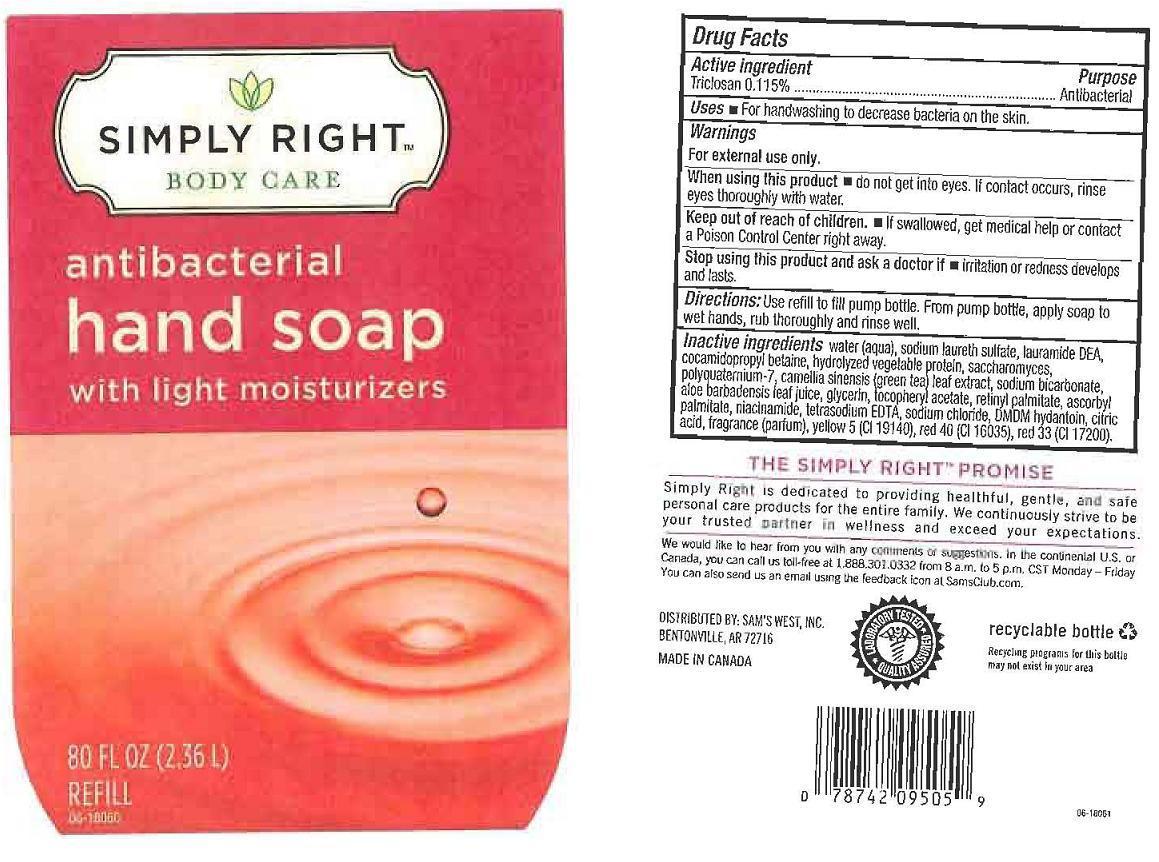 DRUG LABEL: SIMPLY RIGHT BODY CARE
NDC: 68196-144 | Form: LIQUID
Manufacturer: SAM'S WEST INC.
Category: otc | Type: HUMAN OTC DRUG LABEL
Date: 20121025

ACTIVE INGREDIENTS: TRICLOSAN 1.15 mg/1 mL
INACTIVE INGREDIENTS: WATER; SODIUM LAURETH SULFATE; LAURIC DIETHANOLAMIDE; COCAMIDOPROPYL BETAINE; SOY PROTEIN; SACCHAROMYCES LYSATE; POLYQUATERNIUM-7 (70/30 ACRYLAMIDE/DADMAC; 1600 KD); GREEN TEA LEAF; SODIUM BICARBONATE; ALOE VERA LEAF; GLYCERIN; .ALPHA.-TOCOPHEROL ACETATE; VITAMIN A PALMITATE; ASCORBYL PALMITATE; NIACINAMIDE; EDETATE SODIUM; SODIUM CHLORIDE; DMDM HYDANTOIN; CITRIC ACID MONOHYDRATE; FD&C YELLOW NO. 5; FD&C RED NO. 40; D&C RED NO. 33

DRUG FACTS

ACTIVE INGREDIENT

TRICLOSAN 0.115%

PURPOSE

ANTIBACTERIAL

USES

FOR HANDWASHING TO DECREASE BACTERIA ON THE SKIN.

WARNINGS

FOR EXTERNAL USE ONLY.

WHEN USING THIS PRODUCT

DO NOT GET INTO EYES. IF CONTACT OCCURS, RINSE EYES THOROUGHLY WITH WATER.

KEEP OUT OF REACH OF CHILDREN

IF SWALLOWED, GET MEDICAL HELP OR CONTACT A POISON CONTROL CENTER IMMEDIATELY.

STOP USING THIS PRODUCT AND ASK A DOCTOR IF

IRRITATION OR REDNESS DEVELOPS AND LASTS.

DIRECTIONS

USE REFILL TO FILL PUMP BOTTLE. FROM PUMP BOTTLE, APPLY SOAP TO WET HANDS, RUB THOROUGHLY AND RINSE WELL.

INACTIVE INGREDIENTS

WATER (AQUA), SODIUM LAURETH SULFATE, LAURAMIDE DEA, COCAMIDOPROPYL BETAINE, HYDROLYZED VEGETABLE PROTEIN, SACCHAROMYCES, POLYQUATERNIUM-7, CAMELLIA SINENSIS (GREEN TEA) LEAF EXTRACT, SODIUM BICARBONATE, ALOE BARBADENSIS LEAF JUICE, GLYCERIN, TOCOPHERYL ACETATE, RETINYL PALMITATE, ASCORBYL PALMITATE, NIACINAMIDE, TETRASODIUM EDTA, SODIUM CHLORIDE, DMDM HYDANTOIN, CITRIC ACID, FRAGRANCE (PARFUM), YELLOW 5 (CI 19140), RED 40 (CI 16035), RED 33 (CI 17200).